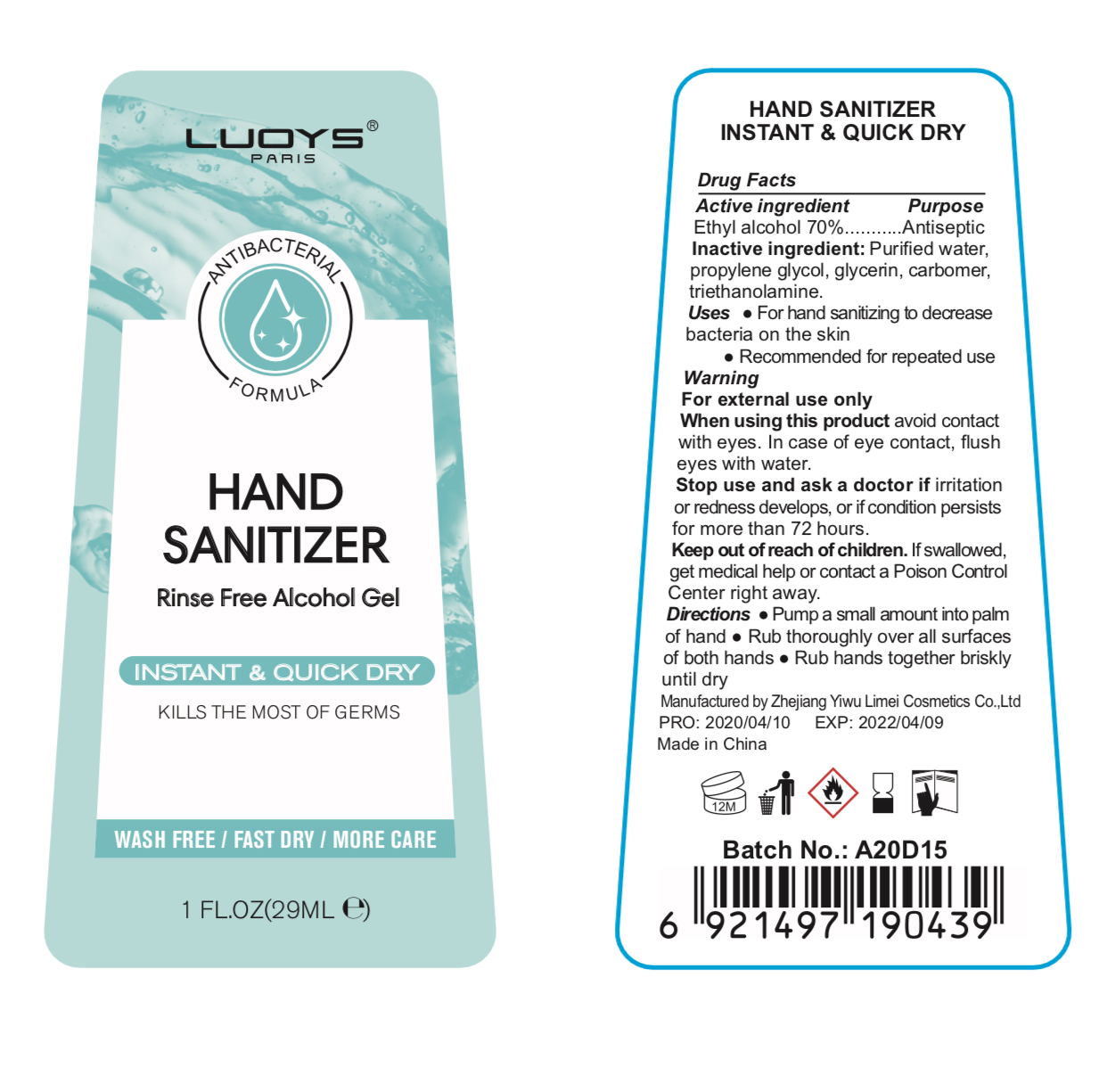 DRUG LABEL: LUOYS Hand Sanitizer
NDC: 74765-003 | Form: GEL
Manufacturer: ZheJiang Yiwu Limei Cosmetics Co., Ltd
Category: otc | Type: HUMAN OTC DRUG LABEL
Date: 20200427

ACTIVE INGREDIENTS: ALCOHOL 70 mL/100 mL
INACTIVE INGREDIENTS: GLYCERIN; PROPYLENE GLYCOL; WATER; CARBOMER 934; TROLAMINE

NA

Active Ingredient(s)

Ethyl Alcohol 70%

Purpose

Antiseptic

Use

For hand sanitizing to help decrease bacteria on the skin

Recommended for repeated use

Warnings

For external use only.

When using this product keep out of eyes. In case of eye contact, flush eyes with water.

Stop use and ask a doctor if irritation or redness develops, or if condition persists for more than 72 hours

Keep out of reach of children. If swallowed, get medical help or contact a Poison Control Center right away.

Directions

- Pump a small amount into palm of hands
- Rub thoroughly over all surface of both hands
- Rub hands together briskly untill dry

Inactive ingredients

Water, propylene glycol, glycerin, carbomer, triethanolamine